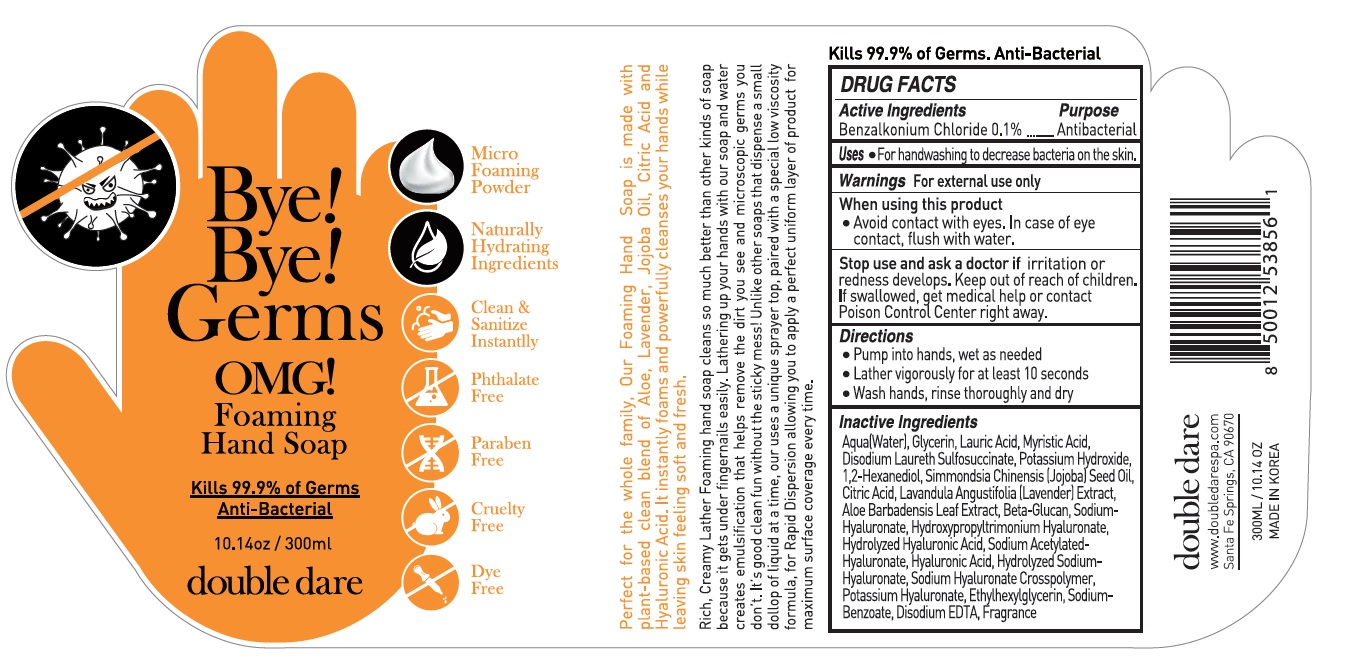 DRUG LABEL: Bye Bye Germs OMG Hand Foaming
NDC: 73724-004 | Form: SOAP
Manufacturer: JK BEAUTY GROUP, INC.
Category: otc | Type: HUMAN OTC DRUG LABEL
Date: 20200609

ACTIVE INGREDIENTS: BENZALKONIUM CHLORIDE 0.001 mg/1 mL
INACTIVE INGREDIENTS: WATER; GLYCERIN; LAURIC ACID; MYRISTIC ACID; DISODIUM LAURETH SULFOSUCCINATE; POTASSIUM HYDROXIDE; 1,2-HEXANEDIOL; JOJOBA OIL; CITRIC ACID MONOHYDRATE; LAVANDULA ANGUSTIFOLIA SUBSP. ANGUSTIFOLIA FLOWERING TOP; ALOE VERA LEAF; HYALURONATE SODIUM; SODIUM ACETYLATED HYALURONATE; HYALURONIC ACID; ETHYLHEXYLGLYCERIN; SODIUM BENZOATE; EDETATE DISODIUM ANHYDROUS

Bye! Bye! Germs OMG! Hand Foaming Soap

Active ingredient

Benzalkonium Chloride 0.1%

Purpose

Antimicrobial

Use

- For handwashing to decrease bacteria on the skin

Warnings

For external use only.

When using this product avoid contact with eyes. In case of eye contact, flush wwith water.

Stop use and ask a doctor if irritation or redness develops.

Keep out of reach of children.

Directions

Pump into hands, wet as needed

Lather vigorously for at least 10 seconds

Wash hands, rinse thoroughly and dry

Inactive ingredients

Water, Glycerin, Lauric Acid, Myristic Acid, Disodium Laureth Sulfosuccinate, Potassium Hydroxide, 1,2-Hexanediol, Simmondsia Chinensis (Jojoba) Seed Oil, Citric Acid, Lavandula Angustifolia (Lavender) Extract, Aloe Barbadensis Leaf Extract, Beta-Glucan, Sodium Hyaluronate , Hydroxypropyltrimonium Hyaluronate, Hydrolyzed Hyaluronic Acid, Sodium Acetylated Hyaluronate, Hyaluronic Acid, Hydrolyzed Sodium Hyaluronate, Sodium Hyaluronate Crosspolymer, Potassium Hyaluronate, Ethylhexylglycerin, Sodium Benzoate, Disodium EDTA, Fragrance